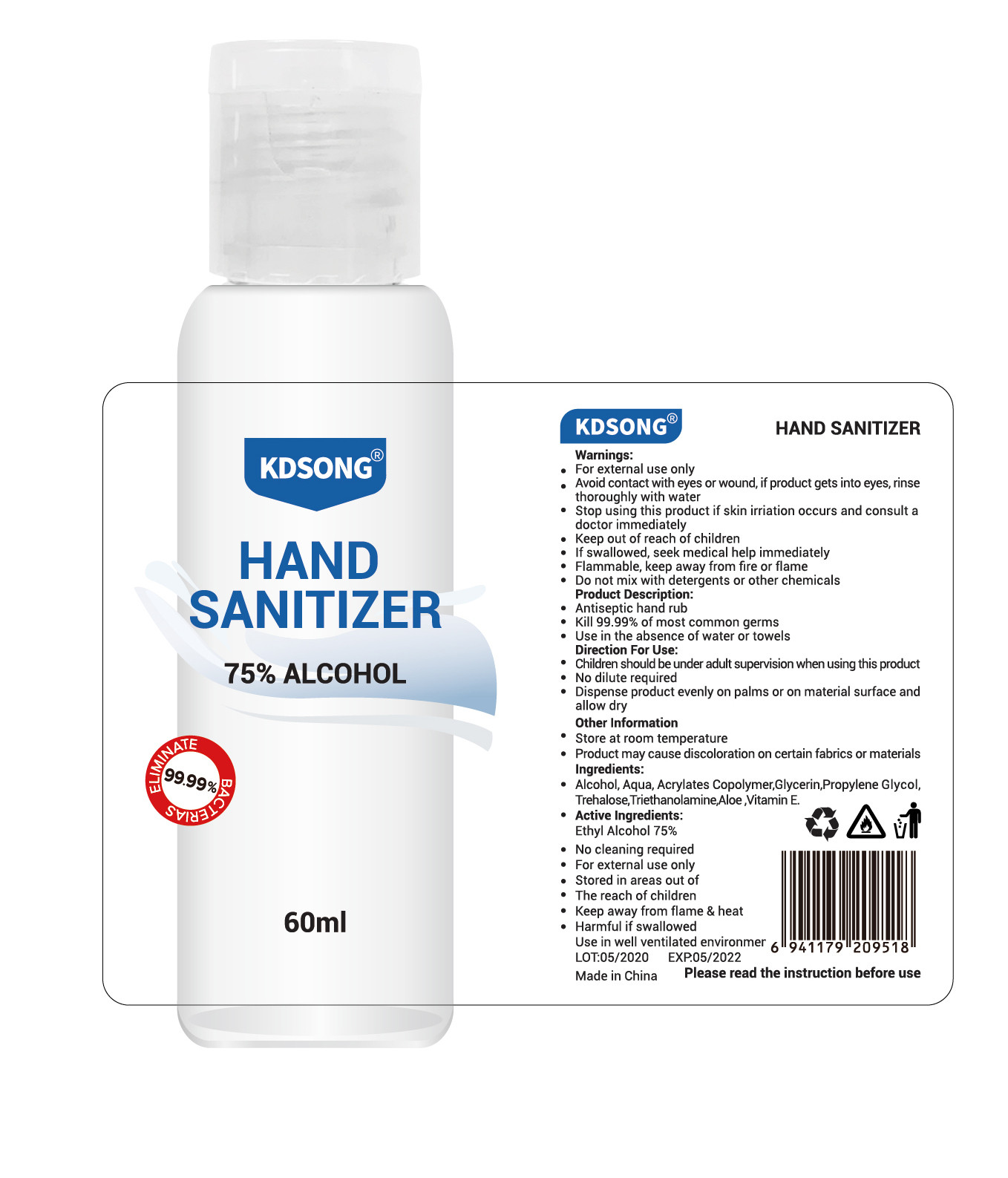 DRUG LABEL: HAND SANIZITER
NDC: 54457-004 | Form: LIQUID
Manufacturer: Guangzhou Zunai Daily Cosmetics Co.,Ltd
Category: otc | Type: HUMAN OTC DRUG LABEL
Date: 20200526

ACTIVE INGREDIENTS: ALCOHOL 45 mL/60 mL
INACTIVE INGREDIENTS: GLYCERIN; WATER; CUPRIC BIS(TRIETHANOLAMINE); BUTYL ACRYLATE/METHYL METHACRYLATE/METHACRYLIC ACID COPOLYMER (18000 MW); PROPYLENE GLYCOL; TREHALOSE

DOSAGE AND ADMINISTRATION

Flammable, keep away from fire or flame，Store at room temperature

INACTIVE INGREDIENT

AQUA

ACRYLATES COPOLYMER

GLYCERIN

PROPYLENE GLYCOL

TREHALOSE

TRIETHANOLAMINE

INDICATIONS AND USAGE

Dispense product evenly on palms or on material surface and allow dry

ACTIVE INGREDIENT

ALCOHOL

keep out of reach of children

PURPOSE

Disinfection
Sterilization
No Rinseing

WARNINGS

1.For external use only,Avoid contact with eyes or wound, if product gets into eyes, rinse thoroughly with water
2.Stop using this product if skin irritation occurs and consult a doctor immediately
3.Keep out of reach of children If swallowed, seek medical help immediately
4.Flammable, keep away from fire or flame
5.Do not mix with detergents or other chemicals